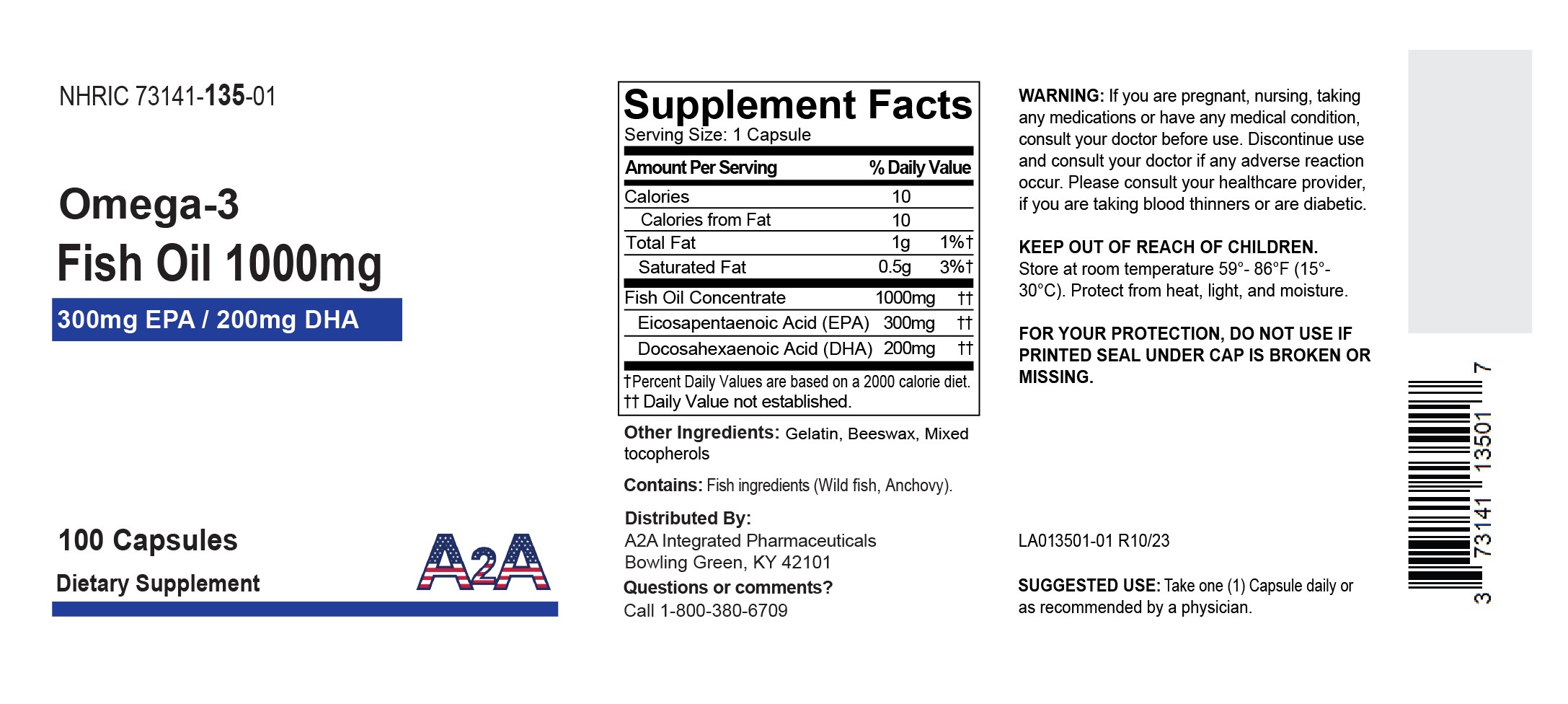 DRUG LABEL: A2A Omega 3
NDC: 73141-135 | Form: CAPSULE
Manufacturer: A2A INTEGRATED PHARMACEUTICALS, LLC
Category: other | Type: DIETARY SUPPLEMENT
Date: 20240122

ACTIVE INGREDIENTS: Icosapent 300 mg/1 1; Doconexent 200 mg/1 1; FISH OIL 1000 mg/1 1
INACTIVE INGREDIENTS: GELATIN, UNSPECIFIED; YELLOW WAX; tocopherol; anchovy, unspecified

OMEGA-3 FISH OIL 1000MG (300MG EPA/200MG DHA)

Supplement Facts

Dietary Supplement

Serving Size: 1 Capsule

 | Amount Per Serving | % Daily Value
Calories | 10
Calories from Fat | 10
Total Fat | 1g | 1%†
Saturated Fat | 0.5g | 3%†
Fish Oil Concentrate Eicosapentaenoic Acid (EPA) Docosahexaenoic Acid (DHA) | 1000mg; 300mg; 200mg | ††; ††; ††
†Percent Daily Values are based on a 2000 calorie diet.
†† Daily Value not established.

Other ingredients: Gelatin, Beeswax, Mixed tocopherols

Contains: Fish ingredients (Wild fish, Anchovy)

SUGGESTED USE

Take one (1) Capsule daily or as recommended by a physician.

WARNING

If you are pregnant, nursing, taking any medications or have any medical condition, consult your doctor before use. Discontinue use and consult your doctor if any adverse reaction occur. Please consult your helathcare provider, if you are taking blood thinners or are diabetic.

KEEP OUT OF REACH OF CHILDREN.

Store at room temperature 59°- 86°F (15°-30°C). Protect from heat, light, and moisture.

FOR YOUR PROTECTION, DO NOT USE IF PRINTED SEAL UNDER CAP IS BROKEN OR MISSING.

Distributed By: A2A Integrated Pharmaceuticals. Bowling Green, KY 42101.

Questions or comments?Call 1-800-380-6709

PRINCIPAL DISPLAY PANEL - 100 Capsule Bottle Label

Omega-3

Fish Oil 1000mg

300mg EPA / 200mg DHA

Dietary Supplement

100 Capsule